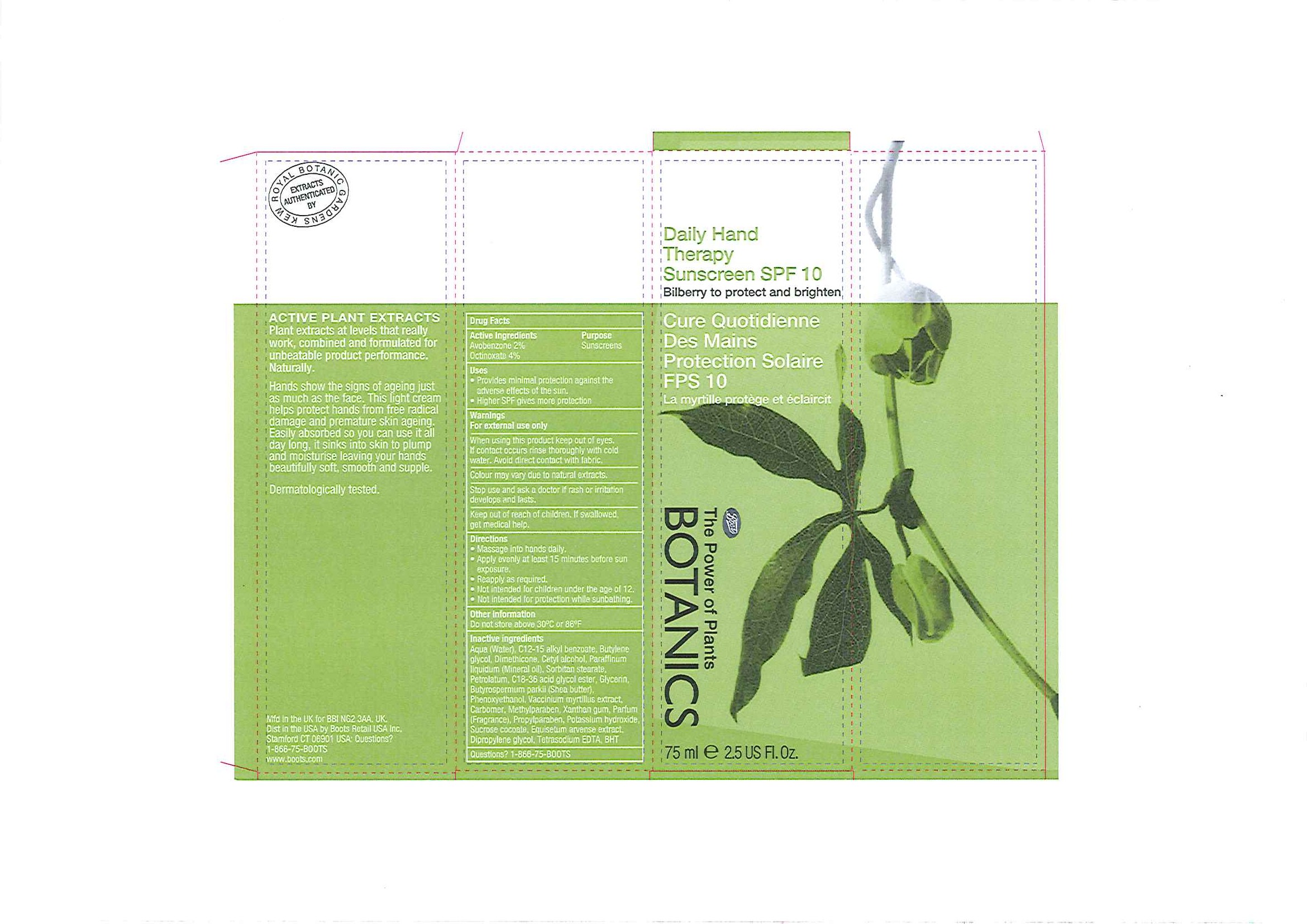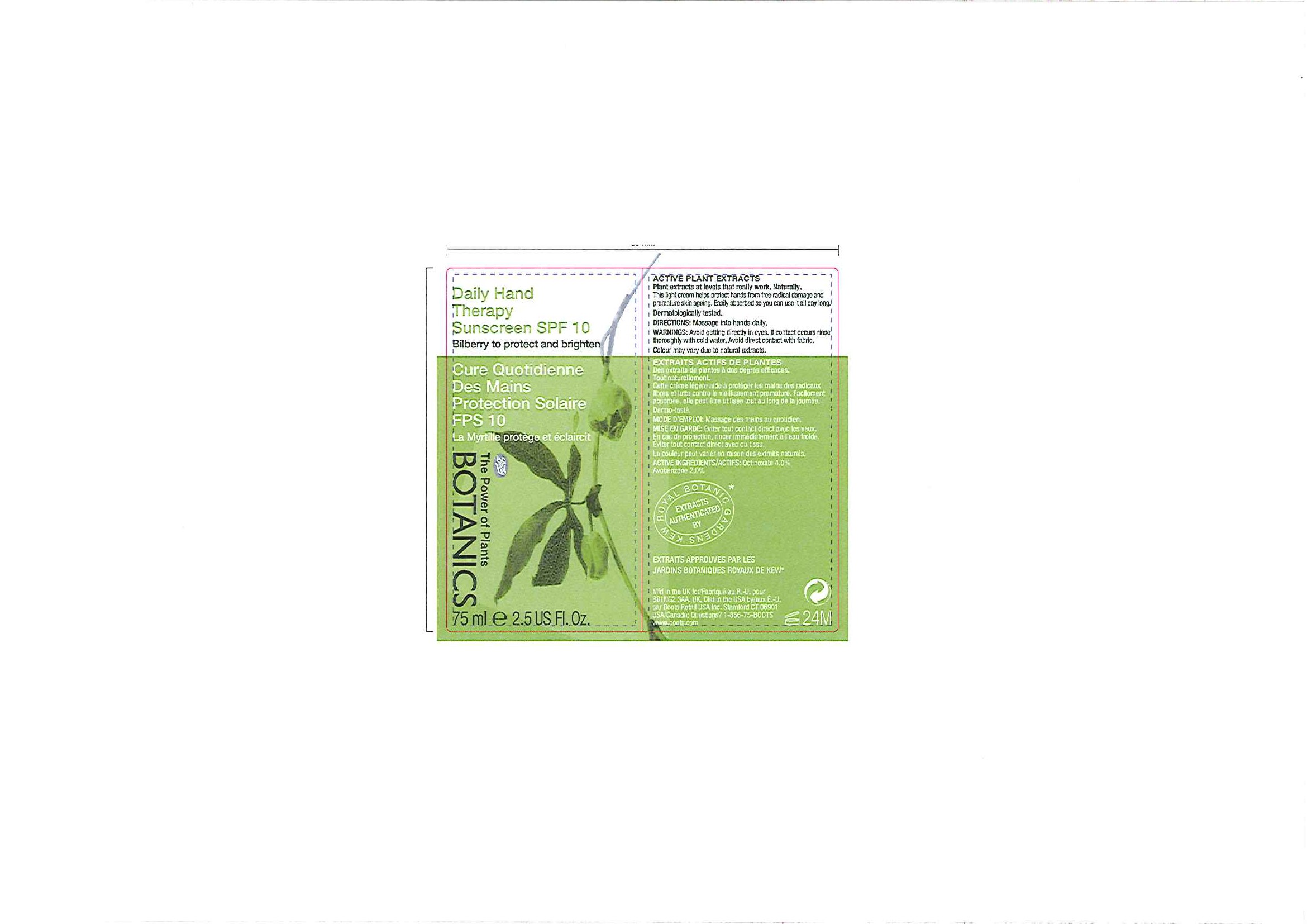 DRUG LABEL: Botanics Daily Hand Therapy Sunscreen SPF 10
NDC: 11489-056 | Form: CREAM
Manufacturer: BCM Ltd
Category: otc | Type: HUMAN OTC DRUG LABEL
Date: 20101207

ACTIVE INGREDIENTS: Octinoxate 3.00 mL/75 mL; Avobenzone 1.5 mL/75 mL
INACTIVE INGREDIENTS: Water; Butylene Glycol; Dimethicone; Cetyl Alcohol; Mineral Oil; Sorbitan Monostearate; Petrolatum; Glycerin; Shea Butter; Phenoxyethanol; Vaccinium Myrtillus Leaf; Carbomer Homopolymer Type C; Methylparaben; Xanthan Gum; Propylparaben; Potassium Hydroxide; Butylated Hydroxytoluene

Carton and tube labelling

Active Ingredients Purpose

Avobenzone 2% Sunscreens

Octinoxate 4%

Uses

- Provides minimal protection against the adverse effects of the sun
- Higher SPF gives more protection

Warnings

For external use only

When using this product keep out of eyes. If contact occurs rinse thoroughly with cold water. Avoid direct contact with fabric.

HOW SUPPLIED

Colour may vary due to natural extracts

Stop use and ask a doctor if rash or irritation develops and lasts.

Keep out of reach of children. If swallowed, get medical help.

Directions

- Massage into hands daily
- Apply evenly at least 15 minutes before sun exposure.
- Reapply as required.
- Not intended for children under the age of 12.
- Not intended for protection while sunbathing.

Other Information

Do not store above 30oC or 86oF.

Inactive ingredients

Aqua (Water), C12-15 alkyl benzoate, Butylene glycol, Dimethicone, Cetyl alcohol, Paraffinum liquidum (Mineral oil), Sorbitan stearate, Petrolatum, C18-36 acid glycol ester, Glycerin, Butyrospermum parkii (Shea butter), Phenoxyethanol, Vaccinium myrtillus extract, Carbomer, Methylparaben, Xanthan gum, Parfum (Fragrance), Propylparaben, Potassium hydroxide, Sucrose cocoate, Equisetum arvense extract, Dipropylene glycol, Tetrasodium EDTA, BHT

USA: Questions? 1-866-75-BOOTS

DESCRIPTION

EXTRACTS AUTHENTICATED BY ROYAL BOTANIC GARDENS KEW

ACTIVE PLANT EXTRACTS

Plant extracts at levels that really work, combined and formulated for unbeatable product performance.

Naturally.

Hands show the signs of ageing just as much as the face. This light cream helps protect hands from free radical damage and premature skin ageing. Easily absorbed so you can use it all day long, it sinks into skin to plump and moisturise leaving your hands beautifully soft, smooth and supple.

Dermatologically tested.

PATIENT COUNSELING INFORMATION

Mfd in the U.K. for BBI NG2 3AA. UK.

Dist in the USA by Boots Retail USA Inc. Stamford CT 06901

USA: Questions? 1-866-75-BOOTS

www.boots.com

DESCRIPTION

Tube label

ACTIVE PLANT EXTRACTS

Plant extract at levels that really work. Naturally.

This light cream helps protect hands from free radical damage and premature skin ageing. Easily absorbed so you can use it all day long.

Dermatologically tested.

EXTRAITS ACTIFS DE PLANTES
Des extraits de plantes à des degrés efficaces. Tout naturellement.
Cette crème légère aide à protéger les main des radicaux libres et lutte contre le vieillissement prematuré. Facilement absorbée, elle peau être utilisée tout au long de la journée.
Dermo-testé

INDICATIONS AND USAGE

DIRECTIONS: Massage into hands daily.

MODE D'EMPLOI: Massage des main au quotidian.

WARNINGS AND PRECAUTIONS

WARNINGS: Avoid getting directly in eyes. If contact occurs rinse thoroughly with cold water. Avoid direct contact with fabric.
MISE EN GARDE: Éviter tout contact avec les yeux. En cas de projection, rincer immédiatement à l'eau froide. Éviter tout contact direct avec du tissu.

HOW SUPPLIED

Colour may vary due to natural extracts.
La couleur peut varier en raison des extraits naturels.

ACTIVE INGREDIENT

ACTIVE INGREDIENTS/ACTIFS: Octinoxate 4.0% Avobenzone 2.0%.

PATIENT COUNSELING INFORMATION

EXTRACTS AUTHENTICATED BY ROYAL BOTANIC GARDENS KEW

EXTRAITS APPROUVES PAR LES JARDINS BOTANIQUES ROYAUX DE KEW

Mfd in the U.K. for/Fabriqué au R.-U. pour BBI NG2 3AA. UK.

Dist in the USA by/aux É.-U. par Boots Retail USA Inc. Stamford CT 06901

USA/Canada: Questions? 1-866-75-BOOTS

www.boots.com

Carton label

Daily Hand Therapy Sunscreen SPF 10

Bilberry to protect and brighten

Cure Quotidienne Des Main Protection Solaire FPS 10

La myrtille protège et éclaircit

Boots

The Power of Plants

Botanics

75ml e 2.5 US Fl. Oz

Daily Hand Therapy carton.jpg

Tube label

Daily Hand Therapy Sunscreen SPF 10

Bilberry to protect and brighten

Cure Quotidienne Des Main Protection Solaire FPS 10

La myrtille protège et éclaircit

Boots

The Power of Plants

Botanics

75ml e 2.5 US Fl. Oz

Daily Hand Therapy label.jpg